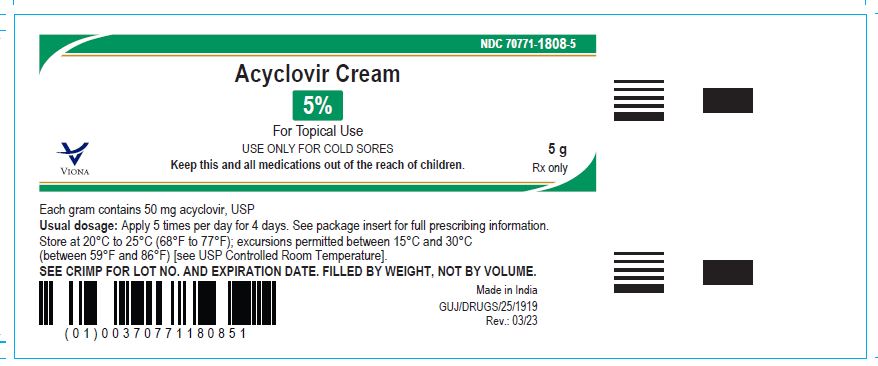 DRUG LABEL: Acyclovir
NDC: 70771-1808 | Form: CREAM
Manufacturer: Zydus Lifesciences Limited
Category: prescription | Type: HUMAN PRESCRIPTION DRUG LABEL
Date: 20240814

ACTIVE INGREDIENTS: ACYCLOVIR 50 mg/1 g
INACTIVE INGREDIENTS: CETOSTEARYL ALCOHOL; MINERAL OIL; PETROLATUM; POLOXAMER 407; PROPYLENE GLYCOL; SODIUM LAURYL SULFATE; WATER

Acyclovir Cream, for topical use

PACKAGE LABEL.PRINCIPAL DISPLAY PANEL

NDC 70771-1808-5 in tube of 5 g

Acyclovir Cream, 5%

Rx only

2 g